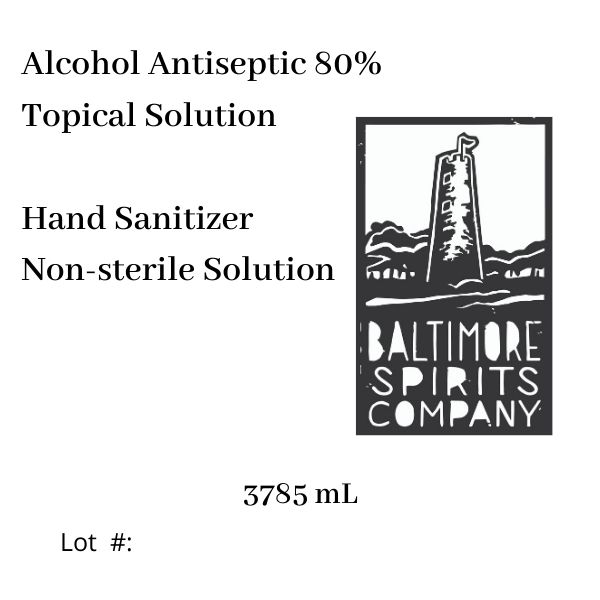 DRUG LABEL: Baltimore Spirits Co Hand Sanitizer
NDC: 73865-000 | Form: LIQUID
Manufacturer: Baltimore Whiskey Company LLC
Category: otc | Type: HUMAN OTC DRUG LABEL
Date: 20200413

ACTIVE INGREDIENTS: ALCOHOL 80 mL/100 mL
INACTIVE INGREDIENTS: GLYCERIN; HYDROGEN PEROXIDE; WATER; DENATONIUM BENZOATE

Alcohol Antiseptic 80% Topical Solution Hand Sanitizer Non-sterile Solution

ACTIVE INGREDIENT

Ethanol 80%

PURPOSE

Antiseptic

INDICATIONS AND USAGE

Hand Sanitizer to help reduce bacteria that potentially can cause disease. For use when soap and water are not available.

WARNINGS

For external use only. Flammable. Keep away from heat or flame

DO NOT USE

• in children less than 2 months of age

• on open skin wounds

Stop use and ask a doctor if irritation or rash occurs. These may be signs of a serious condition

Keep out of reach of children. If swallowed, get medical help or contact a Poison Control Center right away.

Directions

• Place enough product on hands to cover all surfaces. Rub hands together until dry.

• Supervise children under 6 years of age when using this product to avoid swallowing

Other information

• Store between 15-30C (59-86F)

• Avoid freezing and excessive heat above 40C (104F)

INACTIVE INGREDIENT

Inactive ingredients denatonium benzoate, glycerin, hydrogen peroxide, purified water USP